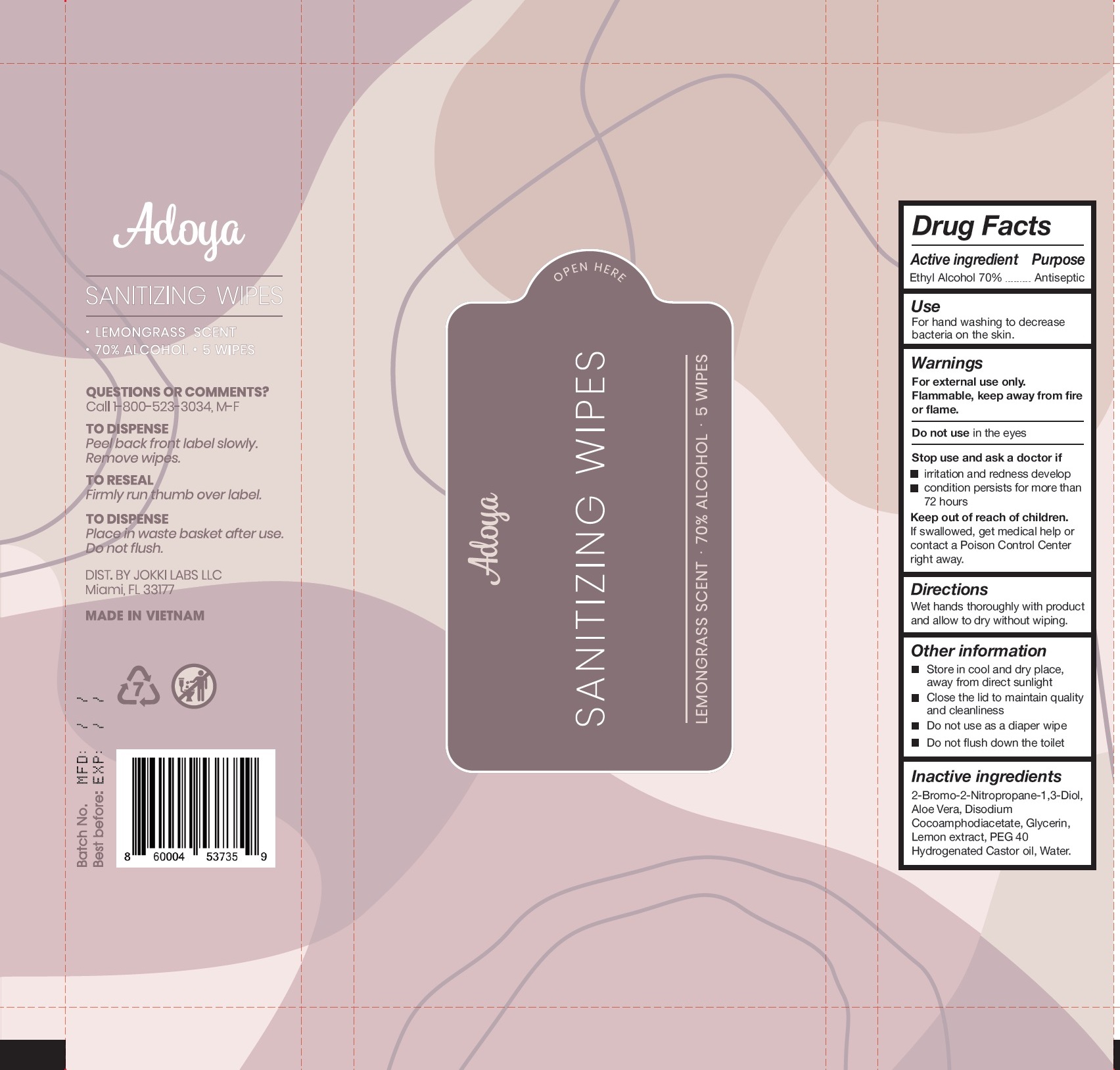 DRUG LABEL: Adoya Sanitizing Wipes
NDC: 79708-001 | Form: CLOTH
Manufacturer: Jokki Labs LLC
Category: otc | Type: HUMAN OTC DRUG LABEL
Date: 20200807

ACTIVE INGREDIENTS: ALCOHOL 0.7 mL/1 mL
INACTIVE INGREDIENTS: BRONOPOL; ALOE VERA LEAF; DISODIUM COCOAMPHODIACETATE; GLYCERIN; LEMON; POLYOXYL 40 HYDROGENATED CASTOR OIL; WATER

Adoya Sanitizing Wipes

Active ingredient

Ethyl Alcohol 70%

Purpose

Antiseptic

Use

For hand washing to decrease bacteria on the skin.

Warnings

For external use only.

Flammable, keep away from fire or flame.

Do not use

in the eyes

Stop ue and ask a doctor if

- irritation and redness develop
- condition persists for more than 72 hours

Keep out of reach of children.

If swallowed, get medical help or contact a Poison Control Center right away.

Directions

Wet hands thoroughly with product and allow to dry without wiping.

Other information

- Store in cool and dry place, away from direct sunlight
- Close the lid to maintain quality and cleanliness
- Do not use as a diaper wipe
- Do not flush down the toilet

Inactive ingredients

2-Bromo-2-Nitropropane-1,3-Diol, Aloe Vera, Disodium Cocoamphodiacetate, Glycerin, Lemon extract, PEG-40 Hydrogenated Castor oil, Water.